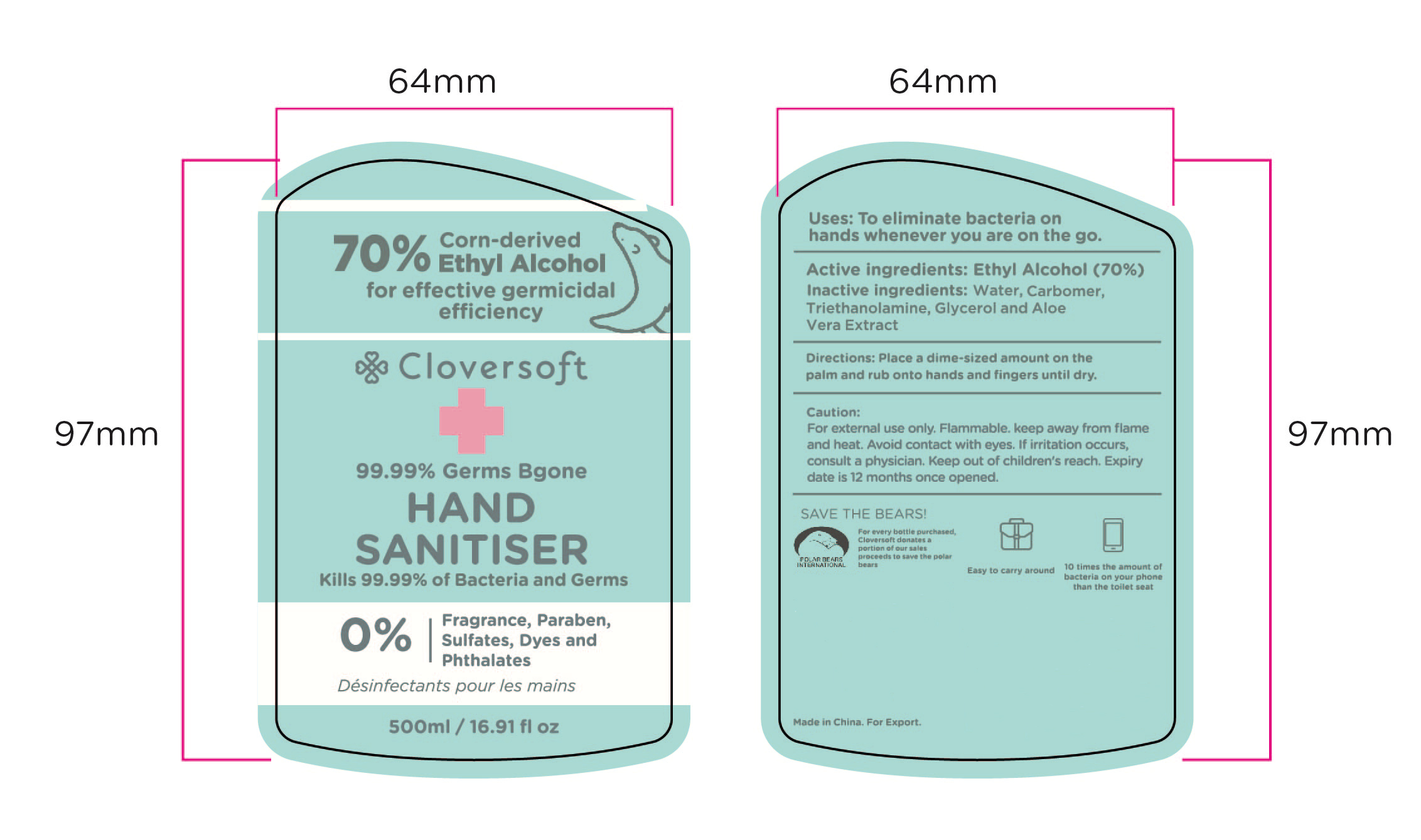 DRUG LABEL: HAND SANITIZER
NDC: 47993-262 | Form: GEL
Manufacturer: NINGBO JIANGBEI OCEAN STAR TRADING CO.,LTD
Category: otc | Type: HUMAN OTC DRUG LABEL
Date: 20201104

ACTIVE INGREDIENTS: ALCOHOL 70 g/112 mL
INACTIVE INGREDIENTS: CARBOMER 940; ALOE VERA LEAF; GLYCERIN; TRIETHANOLAMINE BENZOATE; WATER

47993-262

Uses：

To eliminate bacteria on hands whenever you are on the go.

Active ingredients

Ethyl Alcohol 70%

Inactive Ingredients:

Water,Carbomer,Triethanolamine,Glycerin,Aloe Vera Extract

Directions:

Place a dime-sized amount on the palm and rub onto hands and fingers until dry.

Warnings:

For external use only，Flammable. Keep away from flame and heat. Avoid contact with eyes. If irritation occurs，consult a physician.

Keep out of children’s reach. Expiry date is 12 months once opened.

Keep out of reach of children’s reach.